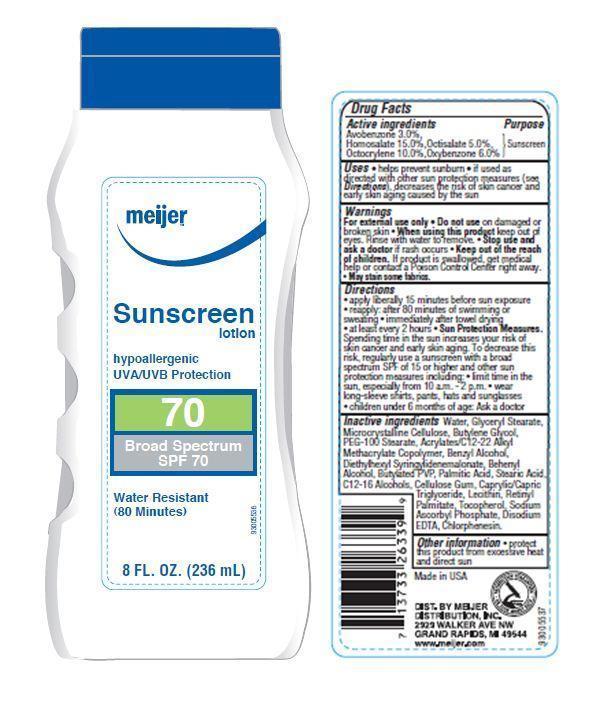 DRUG LABEL: Meijer SPF 70
NDC: 41250-017 | Form: LOTION
Manufacturer: Meijer Distribution Inc
Category: otc | Type: HUMAN OTC DRUG LABEL
Date: 20120101

ACTIVE INGREDIENTS: AVOBENZONE 3 mL/100 mL; HOMOSALATE 15 mL/100 mL; OCTISALATE 5 mL/100 mL; OCTOCRYLENE 10 mL/100 mL; OXYBENZONE 6 mL/100 mL
INACTIVE INGREDIENTS: WATER; GLYCERYL MONOSTEARATE; CELLULOSE, MICROCRYSTALLINE; BUTYLENE GLYCOL; PEG-100 STEARATE; BENZYL ALCOHOL; DIETHYLHEXYL SYRINGYLIDENEMALONATE; DOCOSANOL; PALMITIC ACID; STEARIC ACID; C12-16 ALCOHOLS; CARBOXYMETHYLCELLULOSE SODIUM; MEDIUM-CHAIN TRIGLYCERIDES; LECITHIN, SOYBEAN; VITAMIN A PALMITATE; TOCOPHEROL; SODIUM ASCORBYL PHOSPHATE; EDETATE DISODIUM; CHLORPHENESIN

Drug Facts

Active Ingredients

Avobenzone 3.0% Homosalate 15.0% Octisalate 5.0% Octocrylene 10.0% Oxybenzone 6.0%

Purpose

Sunscreen

Uses

Helps prevent sunburn. If used as directed, with other sun protection measures (see Directions), decreases the risk of skin cancer and early skin aging caused by the sun.

Warnings

For external use only. Do not useon damaged or broken skin.

When using this product

Keep out of eyes. Rinse with water to remove.

Stop use and ask a doctor

if rash occurs

Keep out of reach of children

If swallowed, get medical help or contact a Poison Control Center right away. May stain some fabrics.

Directions

- apply liberally 15 minutes before sun exposure
- reapply
- after 80 minutes of swimming or sweating
- immediately after towel drying
- at least every 2 hours
- Sun Protection Measures: Spending time in the sun increases your risk of skin cancer and early skin aging. To decrease this risk, regularly use a sunscreen with a broad spectrum SPF of 15 or higher and other sun protection measures including:
- limit time in the sun, especially from 10 a.m. - 2 p.m.
- wear long-sleeve shirts, pants, hats and sunglasses
- children under 6 months of age: Ask a doctor

Inactive ingredients

Water, Glyceryl Stearate, Microcrystalline Cellulose, Butylene Glycol, PEG-100 Stearate, Acrylates/C12-22 Alkyl Methacrylate Copolymer, Benzyl Alcohol, Diethylhexyl Syringylidenemalonate, Behenyl Alcohol,Butylated PVP, Palmitic Acid, Stearic Acid, C12-16 Alcohols, Cellulose Gum, Caprylic/Capric Triglyceride, Lecithin, Retinyl Palmitate, Tocopherol, Sodium Ascorbyl Phosphate, Disodium EDTA, Chlorphenesin.

Other Information

protect this product from excessive heat and direct sun